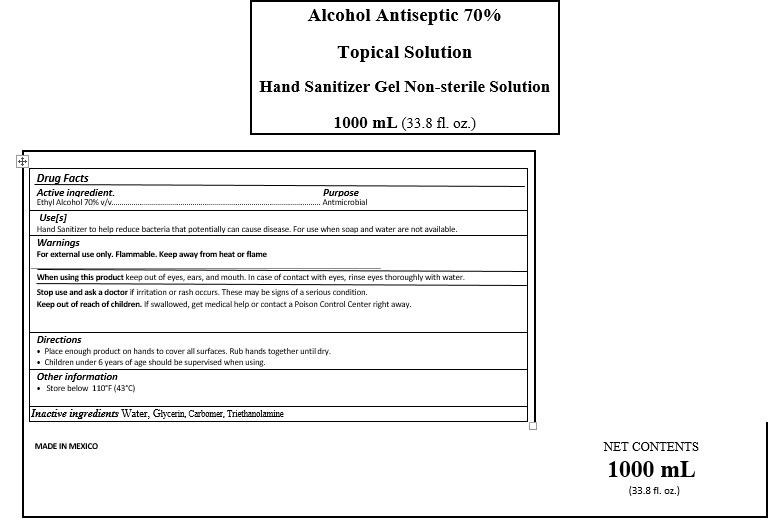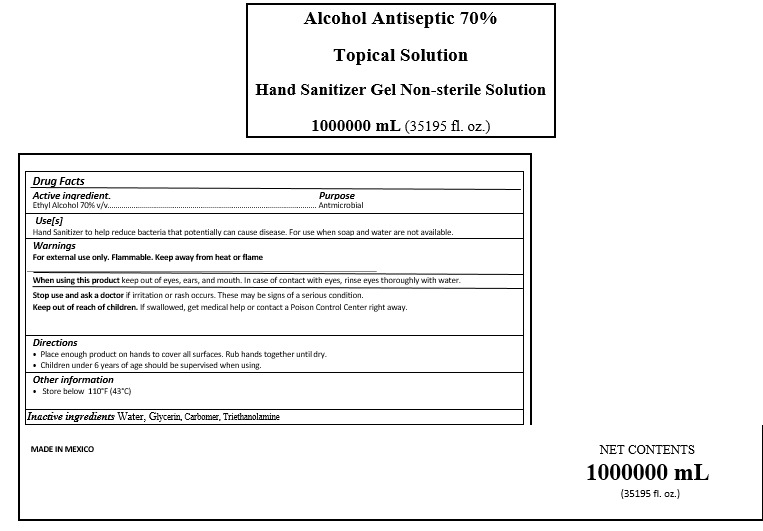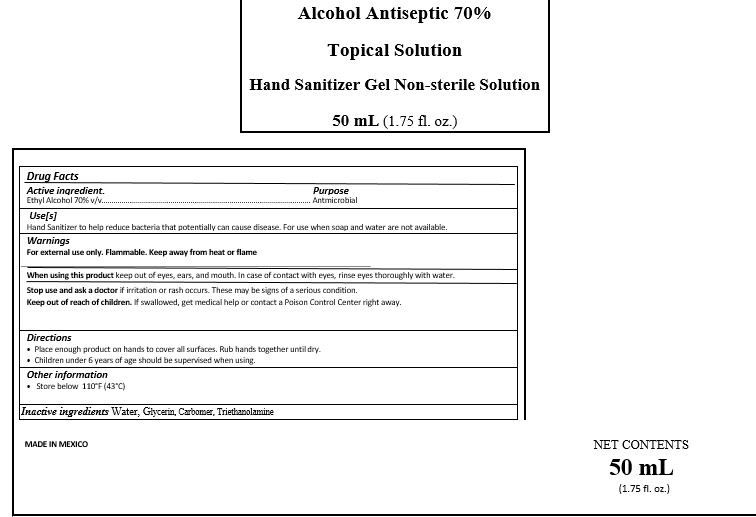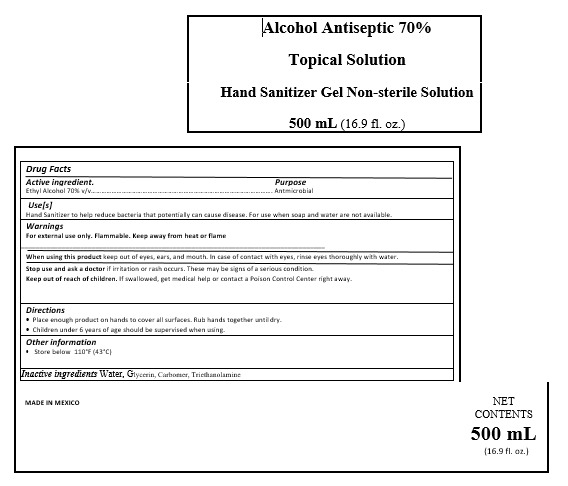 DRUG LABEL: SANGEL
NDC: 80314-0002 | Form: GEL
Manufacturer: ACABADOS GOMAPLUS S.A. DE C.V.
Category: otc | Type: HUMAN OTC DRUG LABEL
Date: 20200826

ACTIVE INGREDIENTS: ALCOHOL 0.7 mL/1 mL
INACTIVE INGREDIENTS: GLYCERIN 0.0031 mL/1 mL; CARBOMER 940 0.0029 mL/1 mL; WATER 0.2914 mL/1 mL; TROLAMINE 0.0026 mL/1 mL

SANGEL HAND SANITIZER GEL

ACTIVE INGREDIENT

Active ingredient. Ethyl Alcohol 70% v/v

PURPOSE

Purpose Antmicrobial

INDICATIONS AND USAGE

Use[s]

Hand Sanitizer to help reduce bacteria that potentially can cause disease. For use when soap and water are not available.

DOSAGE AND ADMINISTRATION

Directions

Place enough product on hands to cover all surfaces. Rub hands together until dry.

WARNINGS AND PRECAUTIONS

When using this product keep out of eyes, ears, and mouth. In case of contact with eyes, rinse eyes thoroughly with water.

Children under 6 years of age should be supervised when using.

WARNINGS

For external use only. Flammable. Keep away from heat or flame

Keep out of reach of children. If swallowed, get

STOP USE

Stop use and ask a doctor if irritation or rash occurs. These may be signs of a serious condition.

INACTIVE INGREDIENTS

Inactive ingredients Water, Glycerin, Carbomer, Triethanolamine